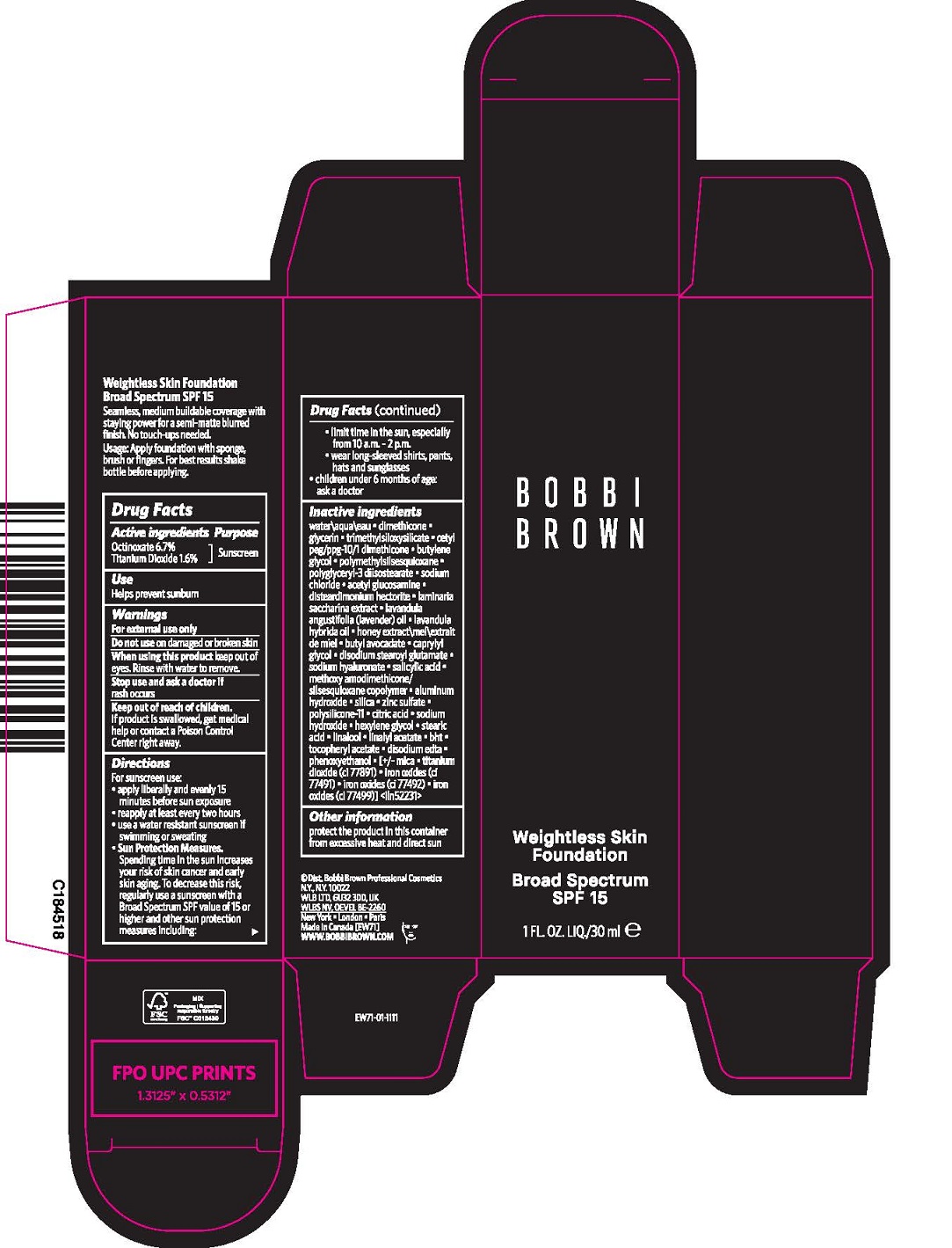 DRUG LABEL: WEIGHTLESS SKIN FOUNDATION BROAD SPECTRUM SPF 15
NDC: 64141-034 | Form: EMULSION
Manufacturer: Bobbi Brown Professional Cosmetics Inc.
Category: otc | Type: HUMAN OTC DRUG LABEL
Date: 20241213

ACTIVE INGREDIENTS: OCTINOXATE 67 mg/1 mL; TITANIUM DIOXIDE 17 mg/1 mL
INACTIVE INGREDIENTS: DISTEARDIMONIUM HECTORITE; SACCHARINA LATISSIMA; BUTYL AVOCADATE; DISODIUM STEAROYL GLUTAMATE; HEXYLENE GLYCOL; FERRIC OXIDE YELLOW; FERROSOFERRIC OXIDE; WATER; LAVANDIN OIL; SALICYLIC ACID; SILICON DIOXIDE; PENTAERYTHRITOL TETRAKIS(3-(3,5-DI-TERT-BUTYL-4-HYDROXYPHENYL)PROPIONATE); LINALOOL, (+/-)-; BUTYLATED HYDROXYTOLUENE; TRIMETHYLSILOXYSILICATE (M/Q 0.8-1.0); POLYMETHYLSILSESQUIOXANE (4.5 MICRONS); POLYGLYCERYL-3 DIISOSTEARATE; SODIUM CHLORIDE; ALUMINUM HYDROXIDE; CETYL PEG/PPG-10/1 DIMETHICONE (HLB 5); N-ACETYLGLUCOSAMINE; CAPRYLYL GLYCOL; HYALURONATE SODIUM; DIMETHICONE/VINYL DIMETHICONE CROSSPOLYMER (SOFT PARTICLE); CITRIC ACID MONOHYDRATE; SODIUM HYDROXIDE; STEARIC ACID; LINALYL ACETATE; ALPHA-TOCOPHEROL ACETATE; MICA; FERRIC OXIDE RED; DIMETHICONE; GLYCERIN; BUTYLENE GLYCOL; LAVENDER OIL; HONEY; EDETATE DISODIUM ANHYDROUS; PHENOXYETHANOL

BOBBI BROWN WEIGHTLESS SKIN FOUNDATION BROAD SPECTRUM SPF 15

ACTIVE INGREDIENTS

OCTINOXATE 6.7%

TITANIUM DIOXIDE 1.6%

PURPOSE

SUNSCREEN

USE

helps prevent sunburn

Warnings

For external use only

Do not use

on damaged or broken skin

When using this product

keep out of eyes. Rinse with water to remove.

Stop use

and ask a doctor if rash occurs

Keep out of reach of children.

If product is swallowed, get medical help or contact a Poison Control Center right away.

Directions

For sunscreen use:

- apply liberally 15 minutes before sun exposure
- reapply at least every two hours
- use a water resistant sunscreen if swimming or sweating
- Sun Protection Measures. Spending time in the sun increases your risk of skin cancer and early skin aging. To decrease this risk, regularly use a sunscreen with a Broad Spectrum SPF value of 15 or higher and other sun protection measures including:
  - limit time in the sun, especially from 10 a.m.–2 p.m.
  - wear long-sleeved shirts, pants, hats and sunglasses
- children under 6 months of age: ask a doctor

Inactive Ingredients

WATER\AQUA\EAU, DIMETHICONE, GLYCERIN, TRIMETHYLSILOXYSILICATE, CETYL PEG/PPG-10/1 DIMETHICONE, BUTYLENE GLYCOL, POLYMETHYLSILSESQUIOXANE, POLYGLYCERYL-3 DIISOSTEARATE, SODIUM CHLORIDE, ACETYL GLUCOSAMINE, DISTEARDIMONIUM HECTORITE, LAMINARIA SACCHARINA EXTRACT, LAVANDULA ANGUSTIFOLIA (LAVENDER) OIL, LAVANDULA HYBRIDA OIL, HONEY EXTRACT\MEL\EXTRAIT DE MIEL, BUTYL AVOCADATE, CAPRYLYL GLYCOL, DISODIUM STEAROYL GLUTAMATE, SODIUM HYALURONATE, SALICYLIC ACID, METHOXY AMODIMETHICONE/SILSESQUIOXANE COPOLYMER, ALUMINUM HYDROXIDE, SILICA, PENTAERYTHRITYL TETRA-DI-T-BUTYL HYDROXYHYDROCINNAMATE, POLYSILICONE-11, CITRIC ACID, SODIUM HYDROXIDE, HEXYLENE GLYCOL, STEARIC ACID, LINALOOL, LINALYL ACETATE, BHT, TOCOPHERYL ACETATE, DISODIUM EDTA, PHENOXYETHANOL, [+/- MICA, TITANIUM DIOXIDE (CI 77891), IRON OXIDES (CI 77491), IRON OXIDES (CI 77492), IRON OXIDES (CI 77499)] <ILN52484>

Other information

protect the product in this container from excessive heat and direct sun

PACKAGE LABEL

BOBBI

BROWN

Weightless Skin

foundation

Broad Spectrum

SPF 15

1FL. OZ. LIQ/30ml e